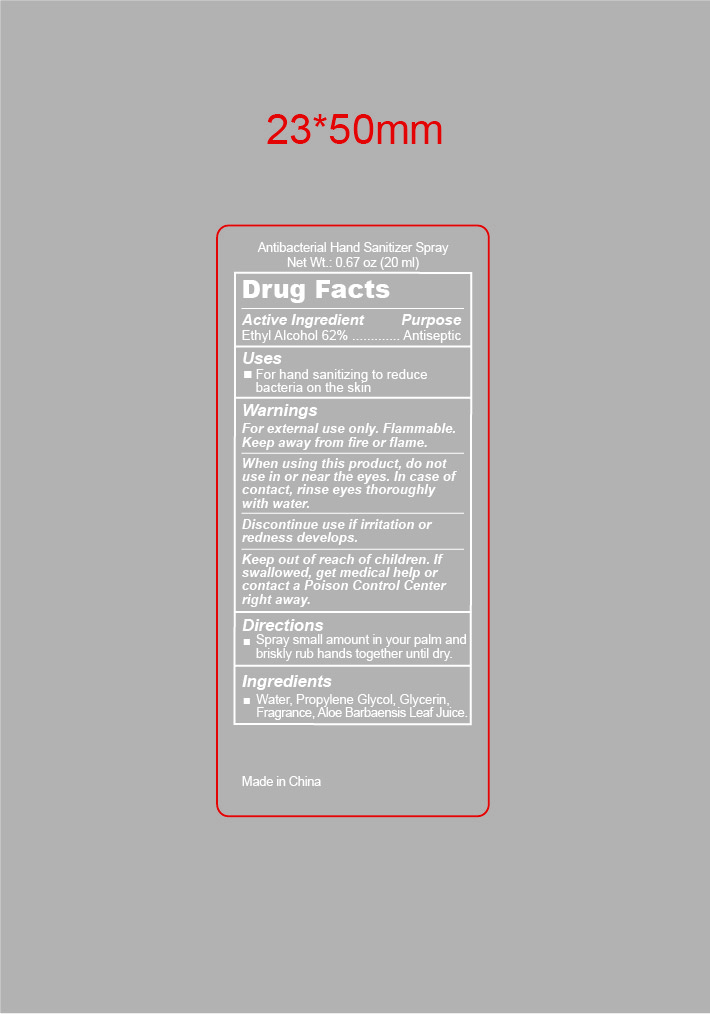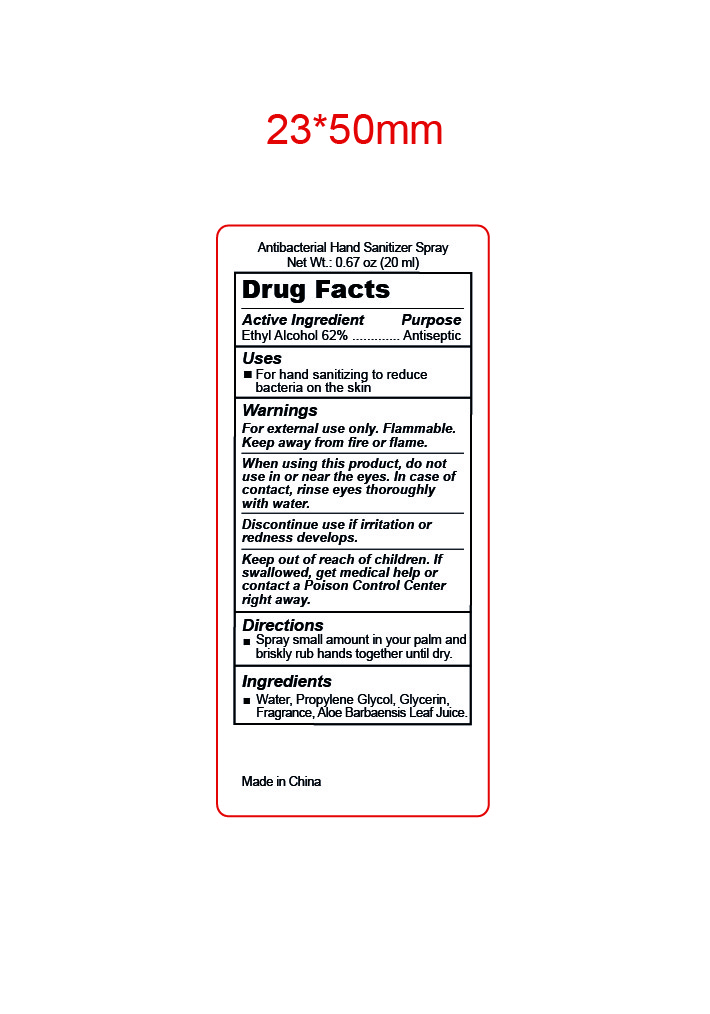 DRUG LABEL: Antibacterial Hand Sanitizer Spray.
NDC: 47993-365 | Form: LIQUID
Manufacturer: NINGBO JIANGBEI OCEAN STAR TRADING CO.,LTD
Category: otc | Type: HUMAN OTC DRUG LABEL
Date: 20240818

ACTIVE INGREDIENTS: ALCOHOL 62 g/112 mL
INACTIVE INGREDIENTS: WATER; PROPYLENE GLYCOL; GLYCERIN; ALOE VERA LEAF

47993-365

Active ingredients

Ethyl Alcohol 62%

PURPOSE

Antiseptic

Uses：

For hand sanitizing to reduce bacteria on the skin.

Warnings:

For external use only.

Flammable. Keep away from fire and flame.

When using this product，do not use in or near the eyes.In case of contact，rinse eyes thoroughly with water.

Discontinue use if irritation or redness develops.

Keep out of reach of children.If swallowed，get medical help or contact a Poison Control Center right away.

Directions:

Spray small amount in your palm and briskly rub hands together until dry.

Inactive Ingredients:

Water，Propylene Glycol，Glycerin，Fragrance，Aloe Barbadensis Leaf Juice.